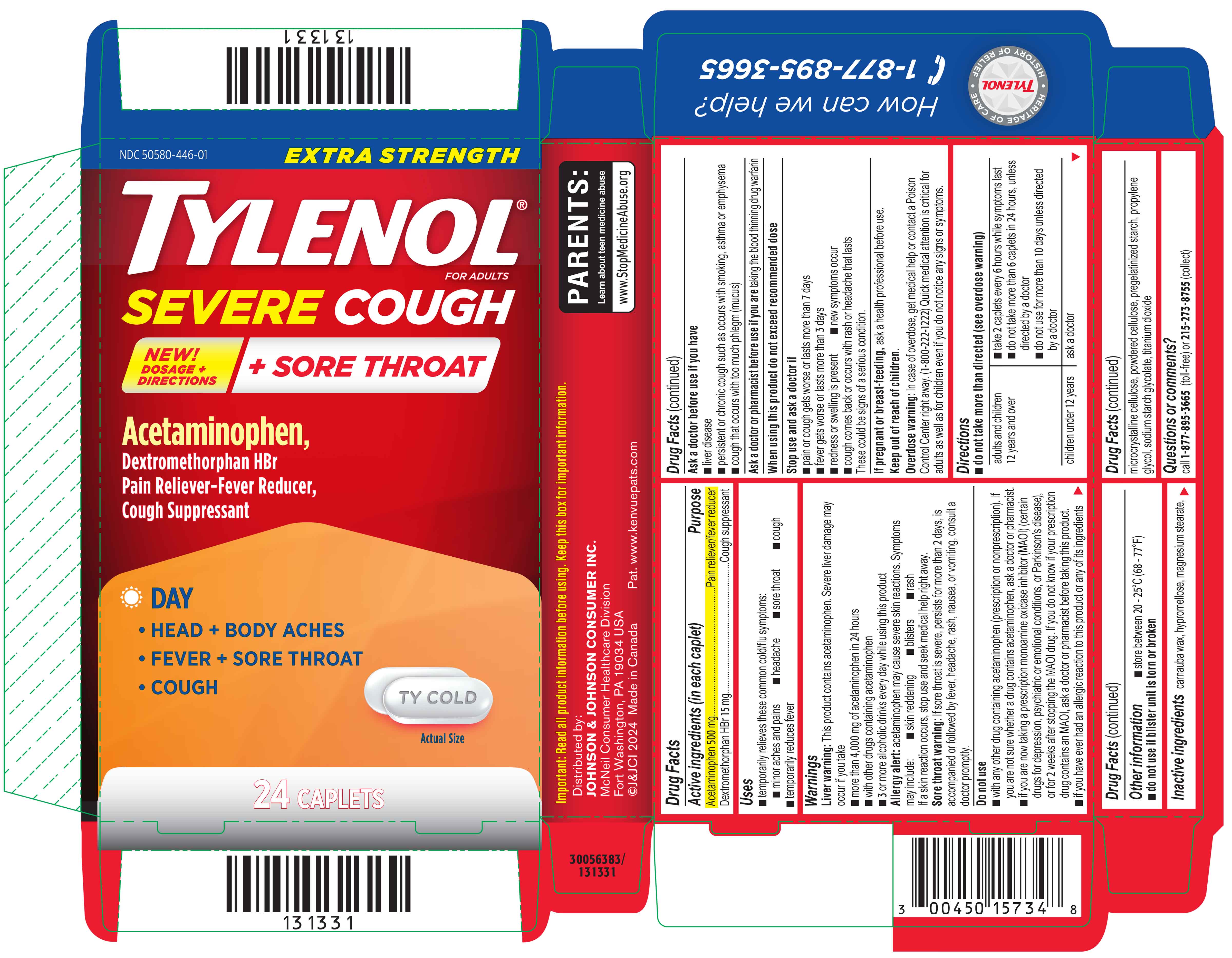 DRUG LABEL: EXTRA STRENGTH TYLENOL SEVERE COUGH PLUS SORE THROAT DAY
NDC: 50580-446 | Form: TABLET, FILM COATED
Manufacturer: Kenvue Brands LLC
Category: otc | Type: HUMAN OTC DRUG LABEL
Date: 20250717

ACTIVE INGREDIENTS: DEXTROMETHORPHAN HYDROBROMIDE 15 mg/1 1; ACETAMINOPHEN 500 mg/1 1
INACTIVE INGREDIENTS: MICROCRYSTALLINE CELLULOSE; MAGNESIUM STEARATE; POWDERED CELLULOSE; PROPYLENE GLYCOL; SODIUM STARCH GLYCOLATE TYPE A; TITANIUM DIOXIDE; CARNAUBA WAX; HYPROMELLOSE, UNSPECIFIED

Extra Strength TYLENOL® Severe Cough + Sore Throat Day

Drug Facts

ACTIVE INGREDIENT

Active ingredients (in each caplet) | Purpose
Acetaminophen 500 mg | Pain reliever/fever reducer
Dextromethorphan HBr 15 mg | Cough suppressant

Uses

- temporarily relieves these common cold/flu symptoms:
  - minor aches and pains
  - headache
  - sore throat
  - cough
- temporarily reduces fever

Warnings

Liver warning

This product contains acetaminophen. Severe liver damage may occur if you take

- more than 4,000 mg of acetaminophen in 24 hours
- with other drugs containing acetaminophen
- 3 or more alcoholic drinks every day while using this product

Allergy alert: acetaminophen may cause severe skin reactions. Symptoms may include:

- skin reddening
- blisters
- rash

If a skin reaction occurs, stop use and seek medical help right away.

Sore throat warning

If sore throat is severe, persists for more than 2 days, is accompanied or followed by fever, headache, rash, nausea, or vomiting, consult a doctor promptly.

Do not use

- with any other drug containing acetaminophen (prescription or nonprescription). If you are not sure whether a drug contains acetaminophen, ask a doctor or pharmacist.
- if you are now taking a prescription monoamine oxidase inhibitor (MAOI) (certain drugs for depression, psychiatric or emotional conditions, or Parkinson's disease), or for 2 weeks after stopping the MAOI drug. If you do not know if your prescription drug contains an MAOI, ask a doctor or pharmacist before taking this product.
- if you have ever had an allergic reaction to this product or any of its ingredients

Ask a doctor before use if you have

■ liver disease

■ persistent or chronic cough such as occurs with smoking, asthma or emphysema

■ cough that occurs with too much phlegm (mucus)

Ask a doctor or pharmacist before use if you are taking the blood thinning drug warfarin

Stop use and ask a doctor if

■ pain or cough gets worse or lasts more than 7 days

■ fever gets worse or lasts more than 3 days

■ redness or swelling is present

■ new symptoms occur

■ cough comes back or occurs with rash or headache that lasts

These could be signs of a serious condition.

PREGNANCY OR BREAST FEEDING

If pregnant or breast-feeding, ask a health professional before use.

Keep out of reach of children.

Overdose warning

In case of overdose, get medical help or contact a Poison Control Center right away. (1-800-222-1222) Quick medical attention is critical for adults as well as for children even if you do not notice any signs or symptoms.

Directions

- do not take more than directed (see overdose warning)

adults and children 12 years and over | - take 2 caplets every 6 hours while symptoms last - do not take more than 6 caplets in 24 hours, unless directed by a doctor - do not use for more than 10 days unless directed by a doctor
children under 12 years | ask a doctor

Other information

- store between 20 - 25°C (68 - 77°F).
- do not use if blister unit is torn or broken

Inactive ingredients

carnauba wax, hypromellose, magnesium stearate, microcrystalline cellulose, powdered cellulose, pregelatinized starch, propylene glycol, sodium starch glycolate, titanium dioxide

Questions or comments?

call 1-877-895-3665 (toll-free) or 215-273-8755 (collect)

PRINCIPAL DISPLAY PANEL

NDC 50580-446-01

EXTRA STRENGTH

TYLENOL®
FOR ADULTS

SEVERE COUGH

+ SORE THROAT

NEW!

DOSAGE + DIRECTIONS

Acetaminophen,
Dextromethorphan HBr

Pain Reliever-Fever Reducer,

Cough Suppressant

DAY

• HEAD + BODY ACHES

• FEVER + SORE THROAT

• COUGH

Actual Size

24 CAPLETS